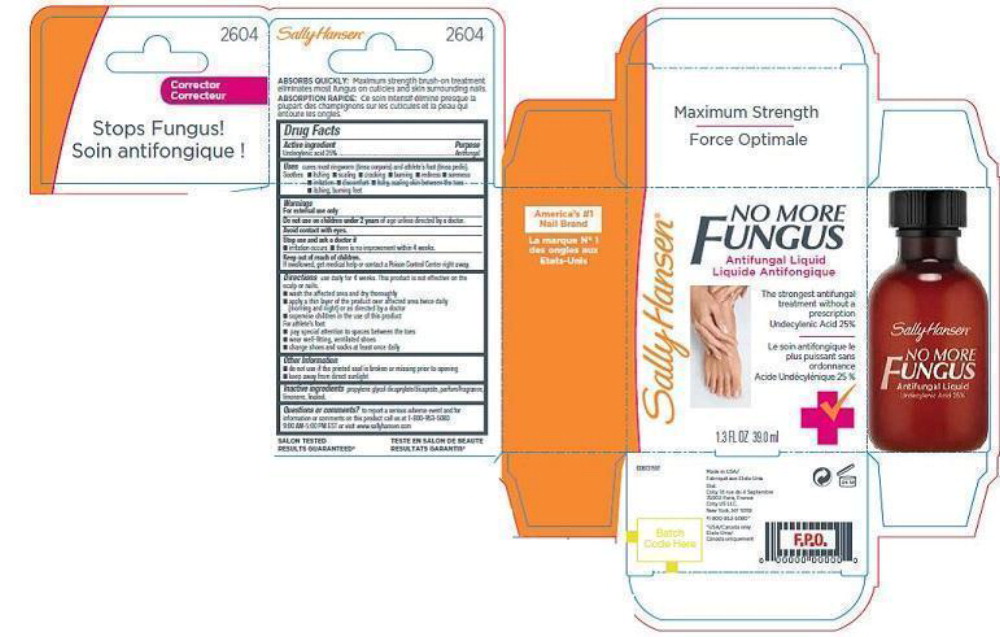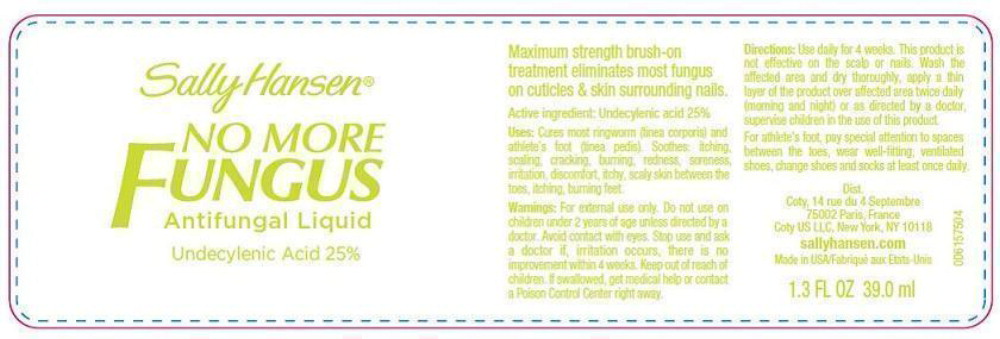 DRUG LABEL: Sally Hansen

NDC: 66184-151 | Form: LIQUID
Manufacturer: Coty US LLC
Category: otc | Type: HUMAN OTC DRUG LABEL
Date: 20211019

ACTIVE INGREDIENTS: UNDECYLENIC ACID 0.23125 g/39.01 mL
INACTIVE INGREDIENTS: PROPYLENE GLYCOL DICAPRYLATE; LIMONENE, (+)-; LINALOOL, (+)-

Active Ingredient

Undecylenic Acid 25%

Purpose

Antifungal

Uses

cures most ringworm (tinea corporis) and athlete's foot (tinea pedis).

Soothes:

- itching
- scaling
- cracking
- burning
- redness
- soreness
- irritation
- discomfort
- itchy, scaling skin between the toes
- itching, burning feet

Warnings

For external use only

Do not use on children under 2 years of age unless directed by a doctor.

Avoid contact with eyes.

Stop use and ask a doctor if:

- irritation occurs
- there is not improvement within 4 weeks.

Keep out of reach of children.

If swallowed, get medical help or contact a Poison Control Center right away.

Directions

Use daily for 4 weeks. This product is not effective on the scalp or nails.

- wash the affected area and dry thoroughly
- apply a thin layer of the product over affected area twice daily (morning and night) or as directed by a doctor
- supervise children in the use of this product

For athlete's foot:

- pay special attention to spaces between the toes
- wear well-fitting, veniltated shoes
- change shoes and socks at least once daily

Other Information

- do not use if the printed seal is broken or missing prior to opening
- keep away from direct sunlight

Inactive ingredients

proplylene glycol dicaprylate/dicaprate, parfum/fragrance, limonene, linalool

Questions or comments?

To report a serious adverse event and for informaiton or comments on this product call us at 1-800-953-5080

9:00AM-5:00PM EST or visit www.sallyhansen.com